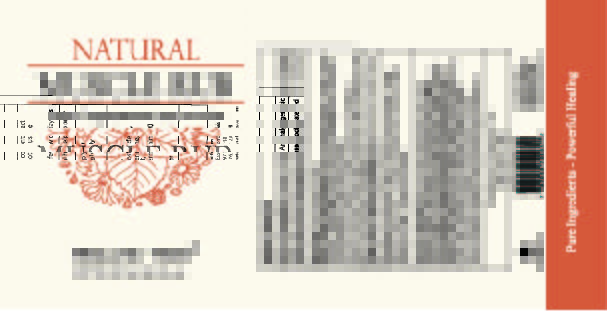 DRUG LABEL: HEALING TREE NATURAL MUSCLE RUB
NDC: 76348-841 | Form: CREAM
Manufacturer: Renu Laboratories, LLC
Category: otc | Type: HUMAN OTC DRUG LABEL
Date: 20250327

ACTIVE INGREDIENTS: MENTHOL 8.74 g/448 g
INACTIVE INGREDIENTS: ALOE VERA LEAF; CALENDULA OFFICINALIS FLOWER; CETOSTEARYL ALCOHOL; MELALEUCA ALTERNIFOLIA (TEA TREE) LEAF OIL; POTASSIUM SORBATE; GLYCERYL MONOSTEARATE; JOJOBA OIL; SODIUM BENZOATE; SODIUM HYDROXIDE; SORBITAN MONOOLEATE; PEG-120 METHYL GLUCOSE DIOLEATE; DECYL GLUCOSIDE; ARNICA MONTANA FLOWER; PEPPERMINT OIL; GLYCERIN; CETYL ALCOHOL; CETEARYL GLUCOSIDE; WATER; EUCALYPTUS OIL; HYPERICUM PERFORATUM

HEALING TREE NATURAL MUSCLE RUB

ACTIVE INGREDIENT

Menthol 1.95%

PURPOSE

External analgesic

Uses

Helps relieve minor muscle and joint pain and soreness associated with sprains, strains, fibromyalgia, and mild arthritis.

Warnings

For external use only

When using this product

- Do not bandage tightly
- avoid contact with eyes
- do not apply to open wounds or damaged skin
- do not use with heating pads or other heating devices

Stop use and ask a doctor if

Condition worsens or

if symptoms persist for more then 7 days or

clear up and occur again within a few days

Keep out of reach of children

If swallowed, get medical help or contact a Poison Control Center right away.

Directions

Adults and children 12 years of age and older -

apply liberally to the affected area

- massage into painful area until thoroughly absorbed into skin
- repeat as necessary

Questions or Comments call

800-376-1293

Inactive Ingredients

Aloe barbadensis (Aloe Vera), Arnica Montana (Arnica) Flower Extract, Calendula officinalis (Marigold) Extract, Carbomer, Cetyl Alcohol, Cetearyl Alcohol, Cetearyl Glucoside, Deionized Water, Eucalyptus globulus (Eucalyptus) Leaf Oil, Glycerine, Glyceryl Stearate, Hypericum Perforatum (St. John's Wort) Extract, Melaleuca Alternifolia (Tea Tree) Leaf Oil, Mentha piperita (Peppermint) Leaf Oil, PEG-120 Methyl Glucose Dioleate, Potassium Sorbate, Simmondsia Chinensis (Jojoba) Seed Oil, Sodium Benzoate, Sodium Hydroxide, Sorbitan Oleate, Decylglucoside Crosspolymer

LABEL ART FOR HEALING TREE MUSCLE RUB 16.0 oz.